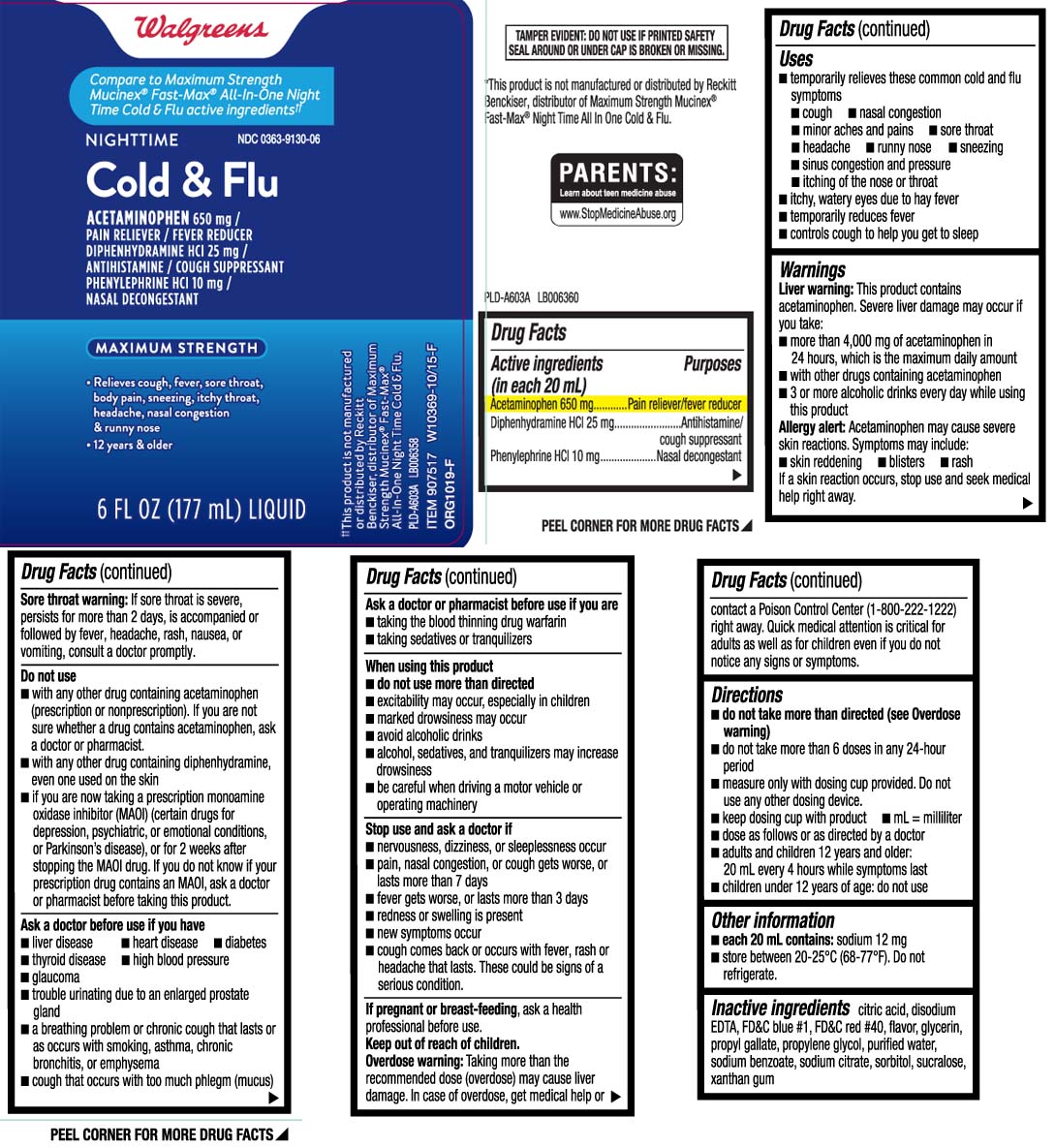 DRUG LABEL: Mucus Relief All in One
NDC: 0363-9130 | Form: LIQUID
Manufacturer: Walgreens
Category: otc | Type: HUMAN OTC DRUG LABEL
Date: 20231010

ACTIVE INGREDIENTS: ACETAMINOPHEN 650 mg/20 mL; DIPHENHYDRAMINE HYDROCHLORIDE 25 mg/20 mL; PHENYLEPHRINE HYDROCHLORIDE 10 mg/20 mL
INACTIVE INGREDIENTS: ANHYDROUS CITRIC ACID; EDETATE DISODIUM; FD&C BLUE NO. 1; FD&C RED NO. 40; GLYCERIN; PROPYL GALLATE; PROPYLENE GLYCOL; WATER; SODIUM BENZOATE; TRISODIUM CITRATE DIHYDRATE; SORBITOL; SUCRALOSE; XANTHAN GUM

Drug Facts

Active ingredients (in each 20 mL)

Acetaminophen 650 mg

Diphenhydramine HCl 25 mg

Phenylephrine HCl 10 mg

Purposes

Pain reliever/fever reducer

Antihistamine/Cough suppressant

Nasal decongestant

Uses

- temporarily relieves these common cold and flu symptoms:
  - cough
  - nasal congestion
  - minor aches and pains
  - sore throat
  - headache
  - runny nose
  - sneezing
  - sinus congestion and pressure
  - itching of the nose or throat
- itchy, watery eyes due to hay fever
- temporarily reduces fever
- controls cough to help you get to sleep

Warnings

Liver warnings: This product contains acetaminophen. Severe liver damage may occur if you take:

- more than 4,000 mg of acetaminophen in 24 hours
- with other drugs containing acetaminophen
- 3 or more alcoholic drinks daily while using this product

Allergy alert: Acetaminophen may cause severe skin reactions. Symptoms may include:

- skin reddening
- blisters
- rash

If a skin reaction occurs, stop use and seek medical help right away.

Sore throat warning: If sore throat is severe, persists for more than 2 days, is accompanied or followed by fever, headache, rash, nausea or vomiting, consult a doctor promptly.

Do not use

- with any other drug containing acetaminophen (prescription or nonprescription). If you are not sure whether a drug contains acetaminophen, ask a doctor or pharmacist.
- with any other drug containing diphenhydramine, even one used on the skin
- if you are now taking a prescription monoamine oxidase inhibitor (MAOI) (certain drugs for depression, psychiatric or emotional conditions, or Parkinson's disease), or for 2 weeks after stopping the MAOI drug. If you do not know if your prescription drug contains an MAOI, ask a doctor or pharmacist before taking this product.

Ask a doctor before use if you have

- liver disease
- heart disease
- diabetes
- thyroid disease
- high blood pressure
- glaucoma
- trouble urinating due to an enlarged prostate gland
- a breathing problem or chronic cough that lasts or as occurs with smoking, asthma, chronic bronchitis or emphysema
- cough that occurs with too much phlegm (mucus)

Ask a doctor or pharmacist before use if you are

- taking the blood thinning drug warfarin.
- taking sedatives or tranquilizers

When using this product,

- do not use more than directed
- excitability may occur, especially in children
- marked drowsiness may occur
- avoid alcoholic drinks
- alcohol, sedatives and tranquilizers may increase drowsiness
- be careful when driving a motor vehicle or operating machinery

Stop use and ask a doctor if

- nervousness, dizziness or sleeplessness occur
- pain, nasal congestion, or cough gets worse or lasts more than 7 days
- fever gets worse or lasts more than 3 days
- redness or swelling is present
- new symptoms occur
- cough comes back, or occurs with fever, rash or headache that lasts.

These could be signs of a serious condition.

If pregnant or breast-feeding,

ask a health professional before use.

Keep out of reach of children.

Overdose warning: Taking more than the recommended dose (overdose) may cause liver damage. In case of overdose, get medical help or contact a Poison Control Center (1-800-222-1222) right away. Quick medical attention is critical for adults as well as for children even if you do not notice any signs or symptoms.

Directions

- do not take more than directed (see overdose warning)
- do not take more than 6 doses in any 24-hour period
- measue only with dosing cup provided. Do not use any other dosing device.
- keep dosing cup with product
- mL = milliliter
- dose as follows or as directed by a doctor
- adults and children 12 years of age and older: 20 mL every 4 hours while symptoms last
- children under 12 years of age: do not use

Other information

- each 20 mL contains: sodium 12 mg
- store between 20-25ºC (68-77ºF). Do not refrigerate.

Inactive ingredients

anhydrous citric acid, disodium EDTA,, FD&C blue #1, FD&C red #40, flavor, glycerin, propyl gallate, propylene glycol, purified water, sodium benzoate, sodium citrate, sorbitol, sucralose, xanthan gum

Principal Display Panel

Compare to Maximum Strength Mucinex® Fast-Max® All-in-One Night Time Cold & Flu active ingredients††

NIGHTTIME

Cold &Flu

ACETAMINOPHEN 650 mg /

PAIN RELIEVER / FEVER REDUCER

DIPHENHYDRAMINE HCl 25 mg /

ANTIHISTAMINE / COUGH SUPPRESSANT

PHENYLEPHRINE HCl 10 mg /

NASAL DECONGESTANT

MAXIMUM STRENGTH

- Relieves cough, fever, sore throat,body pain, sneezing, itchy throat, headache, nasal congestion & runny nose
- 12 years & older

FL OZ (mL)

*This product is not manufactured or distributed by Reckitt Benckiser, distributor of Maximum Strength Mucinex® Fast-Max® All-in-One Night Time Cold & Flu.

TAMPER EVIDENT: DO NOT USE IF PRINTED SAFETY SEAL AROUND OR UNDER CAP IS BROKEN OR MISSING.

DISTRIBUTED BY WALGREENS CO.

200 WILMOT RD., DEERFIELD, IL 60015

Package Label

WALGREENS Mucus Relief Nighttime Cold & Flu